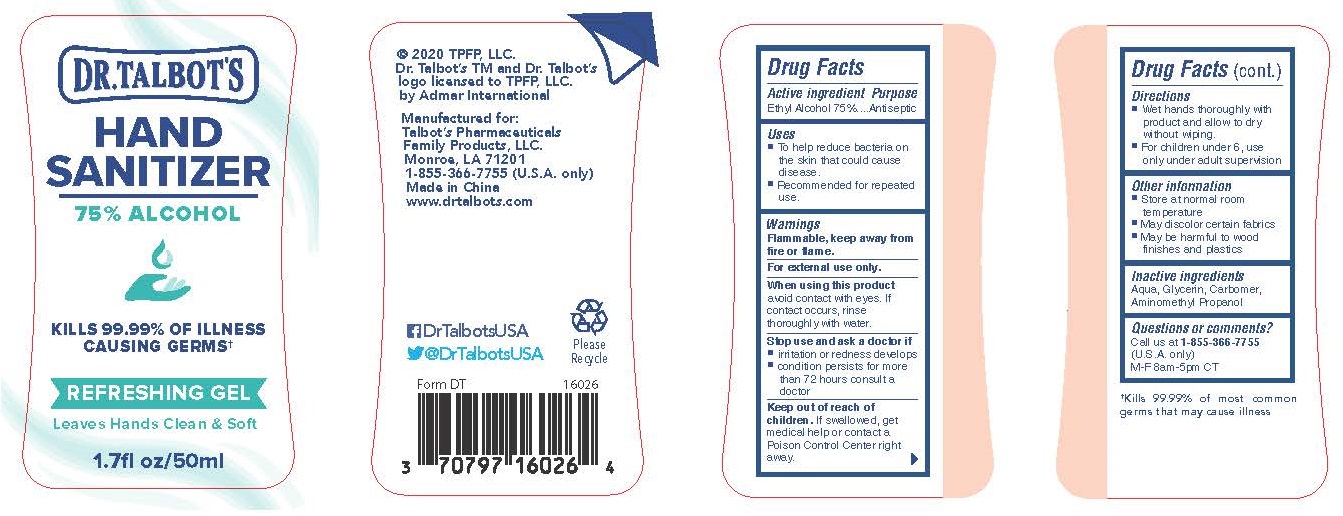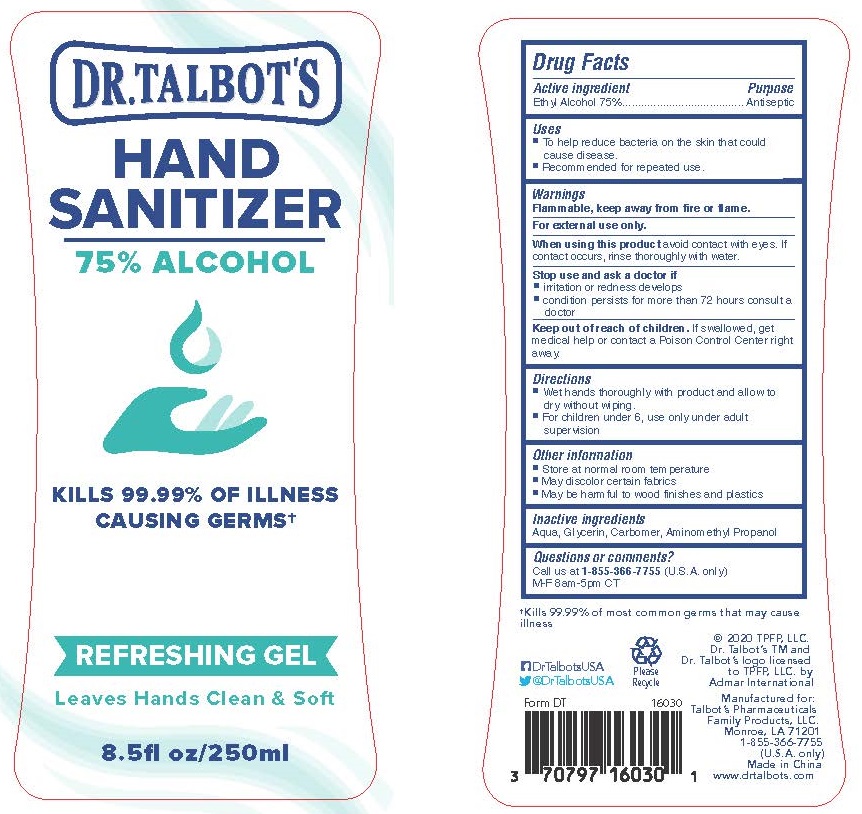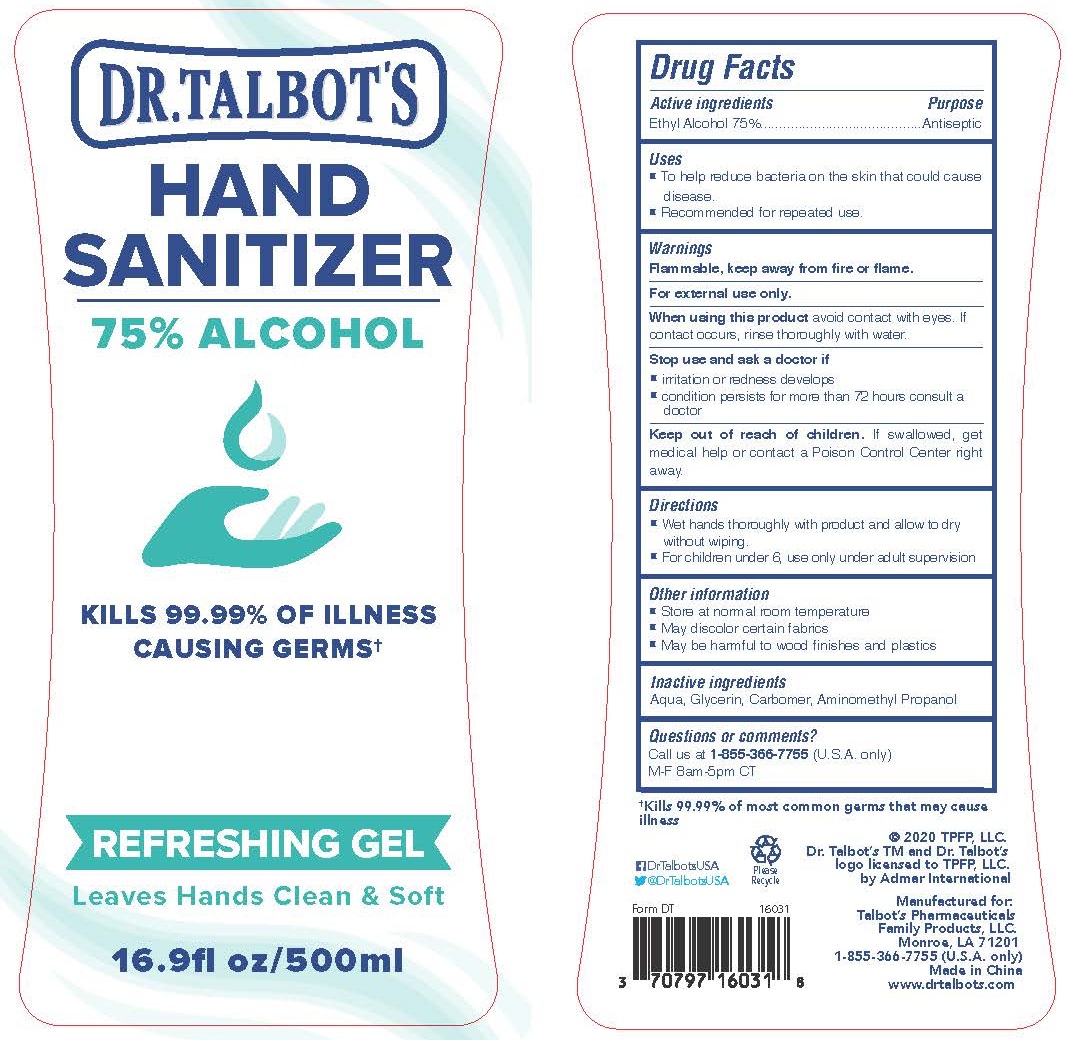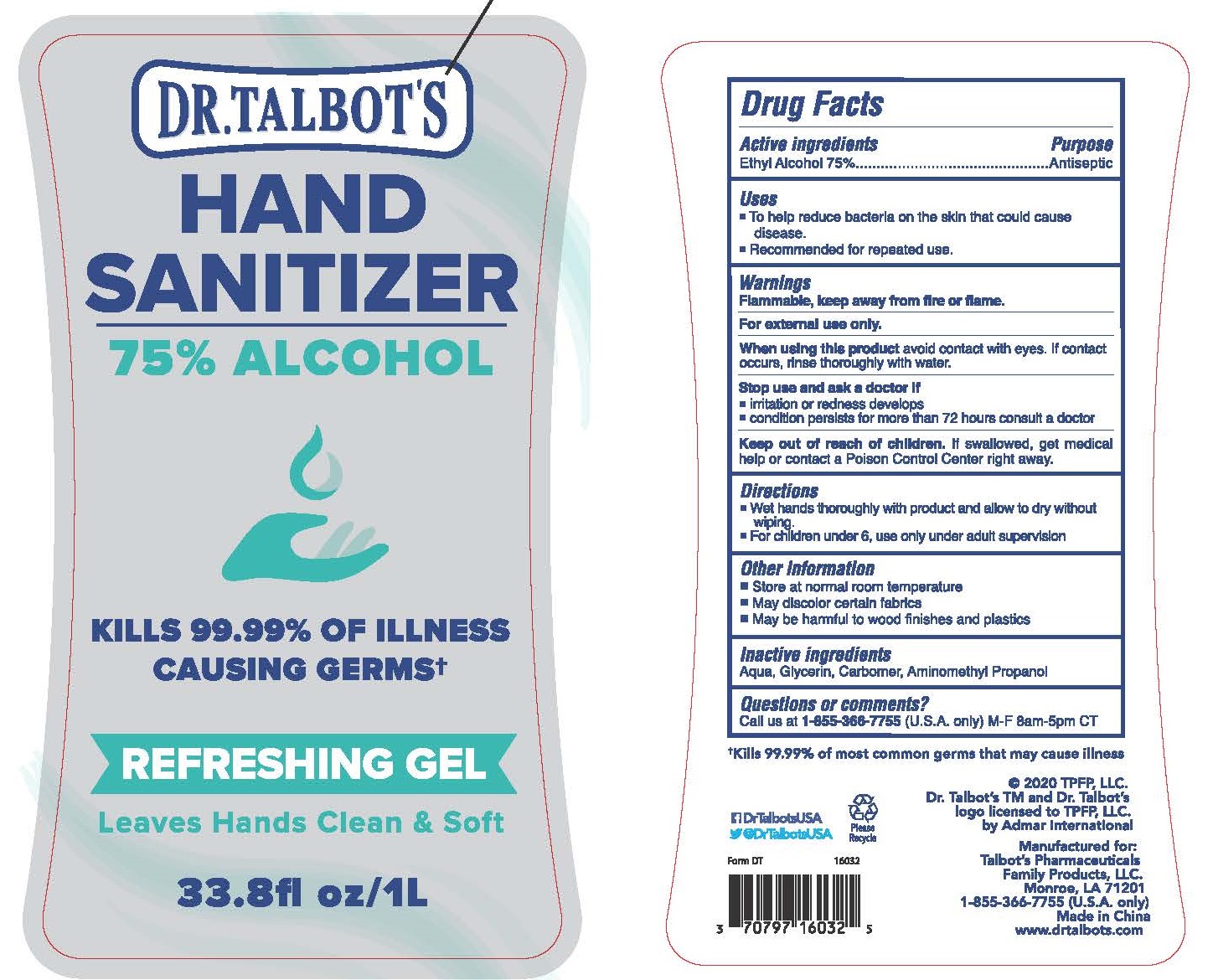 DRUG LABEL: Dr. Talbots
NDC: 70797-160 | Form: GEL
Manufacturer: Talbot’s Pharmaceuticals Family Products, LLC.
Category: otc | Type: HUMAN OTC DRUG LABEL
Date: 20250108

ACTIVE INGREDIENTS: ALCOHOL 75 mL/100 mL
INACTIVE INGREDIENTS: GLYCERIN; WATER; AMINOMETHYL PROPANEDIOL; CARBOMER 934

Purpose

Antiseptic, Hand Sanitizer

Use

To help reduce bacteria on the skin that could cause disease. Recommended for repeated use.

Warnings

For external use only. Flammable. Keep away from heat or flame

When using this product avoid contact with eyes. If contact occurs, rinse thoroughly with water.

Stop use and ask a doctor if irritation or redness develops, condition persists for more than 72 hours consult a doctor.

Keep out of reach of children. If swallowed, get medical help or contact a Poison Control Center right away.

Directions

- Wet hands thoroughly with product and allow to dry without wiping.
- For children under 6, use only under adult supervision.

Other information

- Store at normal room temperature
- May discolor certain fabrics
- May be harmful to wood finishes and plastics

Inactive ingredients

aqua, glycerin, carbomer, aminomethyl propanol

ACTIVE INGREDIENT

Ethyl Alcohol 75%